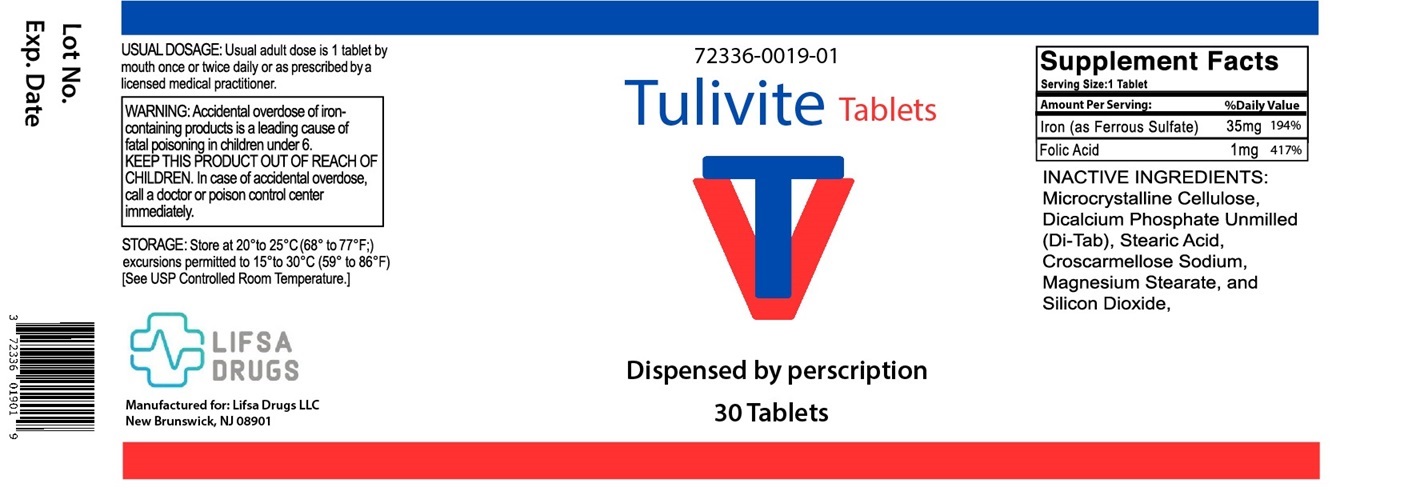 DRUG LABEL: Tulivite
NDC: 72336-019 | Form: TABLET
Manufacturer: Lifsa Drugs LLC
Category: other | Type: Dietary Supplement
Date: 20231129

ACTIVE INGREDIENTS: FERROUS SULFATE 35 mg/1 1; FOLIC ACID 1 mg/1 1
INACTIVE INGREDIENTS: MICROCRYSTALLINE CELLULOSE; ANHYDROUS DIBASIC CALCIUM PHOSPHATE; STEARIC ACID; CROSCARMELLOSE SODIUM; MAGNESIUM STEARATE; SILICON DIOXIDE

Tulivite

HEALTH CLAIM:

TULIVITE Tablets - Dietary Supplement

Dispensed by Prescription

Supplement Facts
Serving Size: 1 Tablet Serving per Bottle: 30
Amount Per Serving: |  | % Daily Value
Iron (as Ferrous Sulfate) | 35 mg | 194%
Folic Acid | 1 mg | 417%

INACTIVE INGREDIENTS: Microcrystalline Cellulose, Dicalcium Phosphate Unmilled (Di-Tab), Stearic Acid, Croscarmellose Sodium, Magnesium Stearate and Silicon Dioxide.

DESCRIPTION:
TULIVITE Tablets is an orally administered prescription vitamin formulation for the clinical dietary management of suboptimal nutritional status in patients where advanced folate supplementation is required and nutritional supplementation in physiologically stressful conditions for maintenance of good health is needed.
CONTRAINDICATIONS:
TULIVITE Tablets are contraindicated in patients with a known hypersensitivity to any of the ingredients. Do not take this product if you are presently taking mineral oil, unless directed by a doctor.

WARNING:

This product is contraindicated in patients with a known hypersensitivity to any of the ingredients.

TULIVITE tablets should only be used under the direction and supervision of a licensed medical practitioner. Use with caution in patients that may have a medical condition, are pregnant, lactating, trying to conceive, under the age of 18, or taking medications.
Accidental overdose of iron-containing products a leading cause of fatal poisoning in children under 6. KEEP THIS PRODUCT OUT OF REACH OF CHILDREN. In case of accidental overdose, call a doctor or poison control center immediately.

Pregnancy and Lactation
TULIVITE is not intended for use in pregnant or lactating patients.

PRECAUTIONS

PRECAUTION:

Folic acid alone is improper therapy in the treatment of pernicious anemia and other megaloblastic anemias where vitamin B is deficient. Folic acid in doses above 1 mg daily may obscure pernicious anemia in that hematologic remission can occur while neurological manifestations progress. TULIVITE Tablets should only be used under the direction and supervision of a licensed medical practitioner.

Do not take within 2 hours of taking oral tetracycline antibiotics, since oral iron products tend to interfere with absorption of tetracycline. May cause gastrointestinal discomfort, nausea, constipation or diarrhea. If you are pregnant or nursing a baby, seek advice of a health professional before using this product. U.S. Consumer Product Safety Commission requires that iron-containing medicine and vitamins with iron be packaged in child-resistant closures. Parents should always use properly re-secure safety closures.

ADVERSE REACTIONS:

Allergic sensitization has been reported following both oral and parenteral administration of folic acid. You may report side effects by calling the FDA at 1-800-FDA-1088.

DOSAGE & ADMINISTRATION:

Usual adult dose is 1 tablet taken orally once or twice daily or as prescribed by a licensed medical practitioner.

HOW SUPPLIED HEALTH CLAIM:

TULIVITE Tablets are available as white, round tablets and are available in 30-count bottles (72336-019-01*). This product is not an Orange Book product.

Dispensed by Prescription†

Manufactured for: Lifsa Drugs LLC, New Brunswick, NJ 08901

Rev. 08/23

*Lifsa Drugs LLC does not represent these product codes to be National Drug Codes (NDC). Product codes are formatted according to standard industry practice, to meet the formatting requirement by pedigree reporting and supply-chain control including pharmacies.

†This product is a prescription-folate with or without other dietary ingredients that – due to increased folate levels increased risk associated with masking of B12 deficiency (pernicious anemia) requires administration under the care of a licensed medical practitioner (61 FR 8760).1-3 The most appropriate way to ensure pedigree reporting consistent with these regulatory guidelines and safety monitoring is to dispense this product only by prescription. This is not an Orange Book product. This product may be administered only under a physician’s supervision and all prescriptions using this product shall be pursuant to state statutes as applicable. The ingredients, indication or claims of this product are not to be construed to be drug claims. 1. Federal Register Notice of August 2, 1973 (38 FR 20750) 2. Federal Register Notice of October 17, 1980 (45 FR 69043, 69044) 3. Federal Register Notice of March 5, 1996 (61 FR 8760)

STORAGE AND HANDLING:

Store at 20°-25°C (68°-77°F); excursions permitted to 15°-30°C (59°-86°F) [See USP Controlled Room Temperature.] Protect from heat, light and moisture. Tamper Evident: Do not use if seal is broken or missing.

Distributed by: Lifsa Drugs LLC, NJ 08901